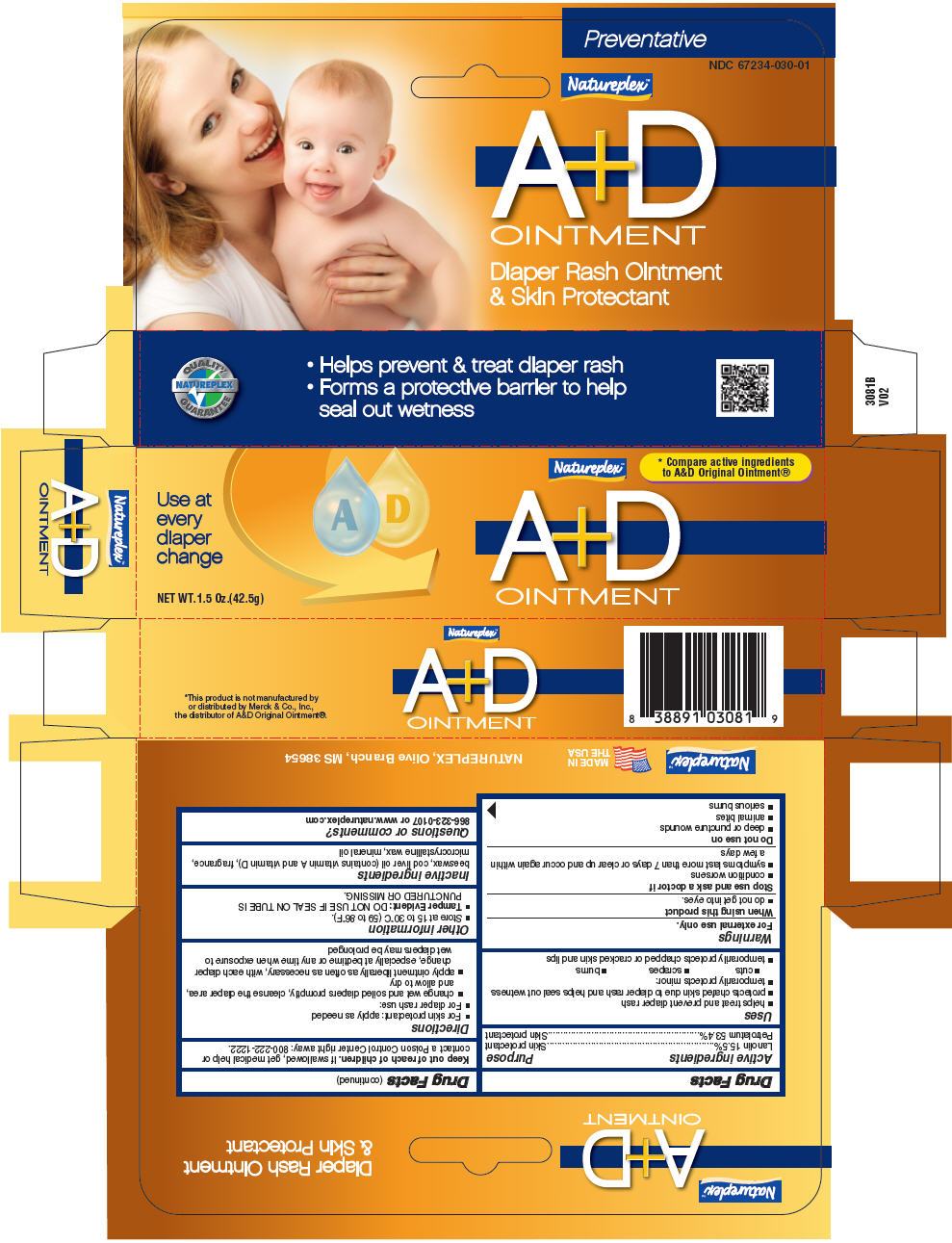 DRUG LABEL: A and D 
NDC: 67234-030 | Form: CREAM
Manufacturer: Natureplex LLC
Category: otc | Type: HUMAN OTC DRUG LABEL
Date: 20241231

ACTIVE INGREDIENTS: Lanolin 0.15 mg/1 g; Petrolatum 0.53 mg/1 g
INACTIVE INGREDIENTS: MINERAL OIL; COD LIVER OIL; MICROCRYSTALLINE WAX; YELLOW WAX

A & D
Diaper Rash and Skin Protectant

Drug Facts

ACTIVE INGREDIENT

Active ingredients | Purpose
Lanolin 15.5% | Skin protectant
Petrolatum 53.4% | Skin protectant

Uses

- helps treat and prevent diaper rash
- protects chafed skin due to diaper rash and helps seal out wetness
- temporarily protects minor:
  - cuts
  - scrapes
  - burns
- temporarily protects chapped or cracked skin and lips

Warnings

For external use only.

When using this product

- do not get into eyes.

Stop use and ask a doctor if

- condition worsens
- symptoms last more than 7 days or clear up and occur again within a few days

Do not use on

- deep or puncture wounds
- animal bites
- serious burns

Keep out of reach of children. If swallowed, get medical help or contact a Poison Control Center right away: 800-222-1222.

Directions

- For skin protectant: apply as needed
- For diaper rash use:
  - change wet and soiled diapers promptly, cleanse the diaper area, and allow to dry
  - apply ointment liberally as often as necessary, with each diaper change, especially at bedtime or any time when exposure to wet diapers may be prolonged

Other information

- Store at 15 to 30°C (59 to 86°F).
- Tamper Evident: DO NOT USE IF SEAL ON TUBE IS PUNCTURED OR MISSING.

Inactive ingredients

beeswax, cod liver oil (contains vitamin A and vitamin D), fragrance, microcrystalline wax, mineral oil

Questions or comments?

866-323-0107 or www.natureplex.com

PRINCIPAL DISPLAY PANEL - 42.5 g Tube Box

Natureplex™

A+D
OINTMENT

* Compare active ingredients
to A&D Original Ointment®

Use at
every
diaper
change

NET WT. 1.5 Oz.(42.5g)